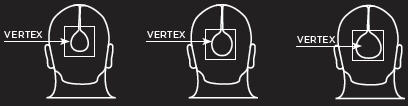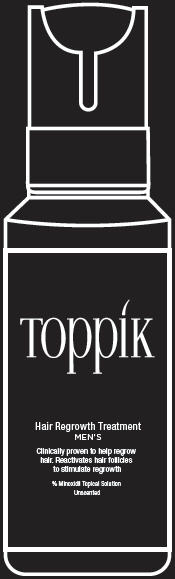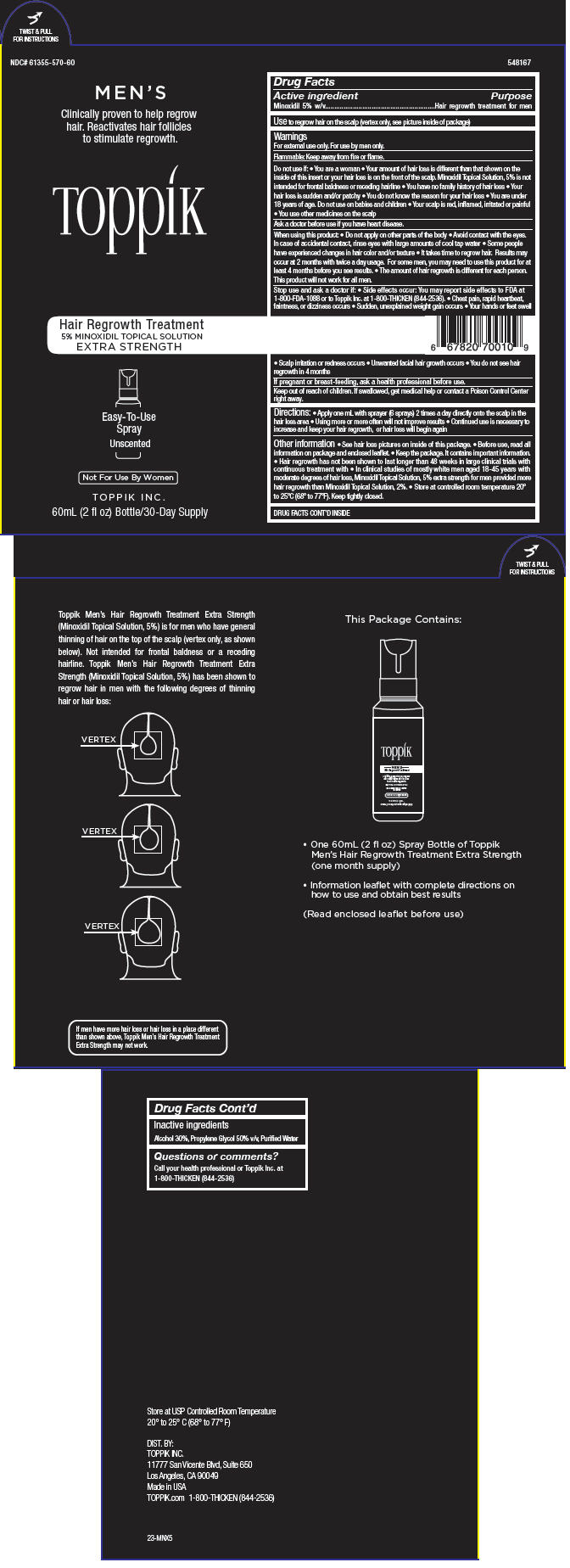 DRUG LABEL: Toppik Mens Hair Regrowth Treatment 
NDC: 61355-570 | Form: SOLUTION
Manufacturer: Spencer Forrest, Inc.
Category: otc | Type: HUMAN OTC DRUG LABEL
Date: 20140506

ACTIVE INGREDIENTS: Minoxidil 50 mg/1 mL
INACTIVE INGREDIENTS: Alcohol; Propylene Glycol; Water

Toppik Men's Hair Regrowth Treatment
Extra Strength

Drug Facts

Active ingredient

Minoxidil 5% w/v

Purpose

Hair regrowth treatment for men

Use

to regrow hair on the scalp (vertex only, see picture inside of package)

Warnings

For external use only. For use by men only.

Flammable: Keep away from fire or flame.

Do not use if:

- You are a woman
- Your amount of hair loss is different than that shown on the inside of this insert or your hair loss is on the front of the scalp. Minoxidil Topical Solution, 5% is not intended for frontal baldness or receding hairline
- You have no family history of hair loss
- Your hair loss is sudden and/or patchy
- You do not know the reason for your hair loss
- You are under 18 years of age. Do not use on babies and children
- Your scalp is red, inflamed, irritated or painful
- You use other medicines on the scalp

Ask a doctor before use if you have heart disease.

When using this product:

- Do not apply on other parts of the body
- Avoid contact with the eyes. In case of accidental contact, rinse eyes with large amounts of cool tap water
- Some people have experienced changes in hair color and/or texture
- It takes time to regrow hair. Results may occur at 2 months with twice a day usage. For some men, you may need to use this product for at least 4 months before you see results.
- The amount of hair regrowth is different for each person. This product will not work for all men.

Stop use and ask a doctor if:

- Side effects occur: You may report side effects to FDA at 1-800-FDA-1088 or to Toppik Inc. at 1-800-THICKEN (844-2536).
- Chest pain, rapid heartbeat, faintness, or dizziness occurs
- Sudden, unexplained weight gain occurs
- Your hands or feet swell
- Scalp irritation or redness occurs
- Unwanted facial hair growth occurs
- You do not see hair regrowth in 4 months

PREGNANCY OR BREAST FEEDING

If pregnant or breast-feeding, ask a health professional before use.

Keep out of reach of children. If swallowed, get medical help or contact a Poison Control Center right away.

Directions

- Apply one mL with sprayer (6 sprays) 2 times a day directly onto the scalp in the hair loss area
- Using more or more often will not improve results
- Continued use is necessary to increase and keep your hair regrowth, or hair loss will begin again

Other information

- See hair loss pictures on inside of this package.
- Before use, read all information on package and enclosed leaflet.
- Keep the package. It contains important information.
- Hair regrowth has not been shown to last longer than 48 weeks in large clinical trials with continuous treatment with
- In clinical studies of mostly white men aged 18-45 years with moderate degrees of hair loss, Minoxidil Topical Solution, 5% extra strength for men provided more hair regrowth than Minoxidil Topical Solution, 2%.
- Store at controlled room temperature 20° to 25°C (68° to 77°F). Keep tightly closed.

Inactive ingredients

Alcohol 30%, Propylene Glycol 50% v/v, Purified Water

Questions or comments?

Call your health professional or Toppik Inc. at 1-800-THICKEN (844-2536)

DIST. BY:
TOPPIK INC.
11777 San Vicente Blvd, Suite 650
Los Angeles, CA 90049

PATIENT INFORMATION

Toppik
Hair Regrowth Treatment
MEN'S
EXTRA STRENGTH
5% Minoxidil Topical Solution
Unscented

Save this leaflet for future reference.

- Provides more hair regrowth than Minoxidil Topical Solution, 2%.
- It takes time to regrow hair. Results may occur at 2 months with twice a day usage. For some men, you may need to use this product for at least 4 months before you see results. Please read this leaflet carefully. It will help you understand how to use Toppik Men's Hair Regrowth Treatment and what to expect from its use. If you have any questions after reading this leaflet, or anytime while using Toppik Men's Hair Regrowth Treatment, you should ask your health care professional or call us at 1-800-THICKEN (844-2536). You can also contact us via email at support@toppik.com or on our website at TOPPIK.com.

What is Toppik Men's Hair Regrowth Treatment Extra Strength?

Toppik Men's Hair Regrowth Treatment is a colorless liquid medication containing 5% minoxidil for use only on the scalp to help regrow hair in men.

Who may use Toppik Men's Hair Regrowth Treatment Extra Strength?

Toppik Men's Hair Regrowth Treatment Extra Strength is for use only by men. Toppik Men's Hair Regrowth Treatment Extra Strength may be appropriate for you if you are a male at least 18 years old and experiencing gradually thinning hair or gradual hair loss on the top of the scalp (vertex only, as shown on the illustration below).

It is not intended for frontal baldness or a receding hairline. The common inherited thinning or hair loss process begins slowly and may become noticeable only after years of gradual loss. Toppik Men's Hair Regrowth Treatment Extra Strength is for men with hair loss or thinning hair that begins on the vertex of the scalp. Toppik Men's Hair Regrowth Treatment Extra Strength is more likely to regrow hair in men with hair loss in the range shown in the diagram. If men have more hair loss than shown, Toppik Men's Hair Regrowth Treatment Extra Strength may not work. Many of those experiencing hair loss have other family members with gradual thinning hair or hair loss. If you have no family history of gradual thinning hair or of gradual hair loss, or your hair loss is patchy, see your doctor.

Who should NOT use Toppik Men's Hair Regrowth Treatment Extra Strength?

- Women should not use Toppik Men's Hair Regrowth Treatment Extra Strength because studies have shown it works no better in women than Women's 2% Minoxidil Topical Solution. Some women may also grow facial hair. In addition, Toppik Men's Hair Regrowth Treatment Extra Strength may be harmful if used during pregnancy or breast-feeding.
- Toppik Men's Hair Regrowth Treatment Extra Strength should not be used on babies or for children under 18 years old.
- Toppik Men's Hair Regrowth Treatment Extra Strength will not prevent or improve hair loss which may occur with the use of some prescription and non-prescription medications, certain severe nutritional problems (very low body iron; too much vitamin A intake), low thyroid states (hypothyroidism), chemotherapy, or diseases which cause scarring of the scalp. Also, Toppik Men's Hair Regrowth Treatment Extra Strength will not improve hair loss due to:
- Damage from the use of hair care products which cause scarring or deep burns of the scalp.
- Hair grooming methods such as cornrowing or ponytails which require pulling the hair tightly back from the scalp.

Do not use if you are not sure of the reason for your hair loss.

Toppik Men's Hair Regrowth Treatment Extra Strength differs from Minoxidil Topical Solution, 2% (Regular Strength) for Women products in the following ways:

- Contains 5% minoxidil (regular strength contains 2%)
- Regrows more hair
- With Toppik Men's Hair Regrowth Treatment Extra Strength results may occur at 2 months with twice a day usage. For some men, you may need to use this product for at least 4 months before you see results.
- Is more likely to cause skin irritation. If scalp irritation continues or worsens, stop use and see a doctor. See Warnings on package or bottle label.

Will Toppik Men's Hair Regrowth Treatment Extra Strength work for me?

The amount of hair regrowth is different for each person. Not everyone will respond to Toppik Men's Hair Regrowth Treatment Extra Strength. The response to Toppik Men's Hair Regrowth Treatment Extra Strength cannot be predicted. It is unlikely anyone will be able to grow back all their hair. However, to see your best results with Toppik Men's Hair Regrowth Treatment Extra Strength, make sure you get the medicine directly to the scalp and apply it twice a day, every day. You may get better results if you have been losing your hair for a short period of time or have little hair loss. However, for some men Toppik Men's Hair Regrowth Treatment Extra Strength may not work.

How soon can I expect results from using Toppik Men's Hair Regrowth Treatment Extra Strength?

Since normal hair usually grows only 1/2 to 1 inch per month, hair regrowth with Toppik Men's Hair Regrowth Treatment Extra Strength also takes time. Results may be seen as early as 2 months with twice daily use. For some men, it may take at least 4 months for results to be seen. If you do not see any results after 4 months, stop using Toppik Men's Hair Regrowth Treatment Extra Strength. When you first begin to use Toppik Men's Hair Regrowth Treatment Extra Strength, your hair loss may increase temporarily for up to 2 weeks. This is likely a sign that you are getting rid of old hairs in order to regrow more new hairs. This temporary increase in hair loss is expected and is a part of the process for how Toppik Men's Hair Regrowth Treatment Extra Strength regrows hair. Remember, this increased hair loss is temporary. However, if it continues after two weeks, see your doctor.

If Toppik Men's Hair Regrowth Treatment Extra Strength is working, what will the hair look like?

At first, hair growth is usually soft, downy, colorless hairs (like peach fuzz). After further use, the new hairs should be the same color and thickness as the other hairs on your scalp.

How long do I need to use Toppik Men's Hair Regrowth Treatment Extra Strength?

If you experience hair regrowth, continued use of Toppik Men's Hair Regrowth Treatment Extra Strength is necessary or the hair loss will begin again. In studies with Minoxidil Topical Solution 5% (Extra Strength), hair regrowth has not been shown to last longer than 48 weeks of continuous treatment in large clinical trials.

What happens if I completely stop using Toppik Men's Hair Regrowth Treatment Extra Strength? Will I keep the new hair?

Continuous use of Toppik Men's Hair Regrowth Treatment Extra Strength is needed to maintain hair regrowth. If you stop using Toppik Men's Hair Regrowth Treatment Extra Strength, you will lose your newly regrown hair in 3 to 4 months.

How do I use Toppik Men's Hair Regrowth Treatment Extra Strength?

For best results, apply 1 mL (6 sprays) 2 times a day directly onto the scalp in the hair loss area. Using more or more often will not improve results. Each bottle should last one month, if used as directed. It is not necessary to use fingertips when applying Toppik Men's Hair Regrowth Treatment. However, if you do uses your fingertips, wash your hands well immediately afterwards. Allow time for Toppik Men's Hair Regrowth Treatment Extra Strength to dry completely before wearing a hat, or lying on a pillow, etc. Toppik Men's Hair Regrowth Treatment Extra Strength may cause staining of clothing or linens if damp on the scalp. When applying Toppik Men's Hair Regrowth Treatment Extra Strength at night, be sure to allow 2 to 4 hours to dry completely. Never take this product by mouth or apply to other parts of the body.

When do I use Toppik Men's Hair Regrowth Treatment Extra Strength?

Apply Toppik Men's Hair Regrowth Treatment Extra Strength once in the morning and once at night. The nighttime application should occur 2 to 4 hours before going to bed to allow for drying. Each bottle should last one month, if used as directed.

What if I miss a dose or forget to use Toppik Men's Hair Regrowth Treatment Extra Strength?

If you miss one or two daily doses of Toppik Men's Hair Regrowth Treatment Extra Strength, just continue with your next dose. You should not make up for missed doses.

Can I use Toppik Men's Hair Regrowth Treatment Extra Strength more than twice a day? Will it work faster, better?

No. Toppik Men's Hair Regrowth Treatment Extra Strength will not work faster or better if used more than two times a day. Studies have been carefully conducted to determine the correct amount of Toppik Men's Hair Regrowth Treatment Extra Strength needed to get the best results. More frequent use or larger doses have not been shown to speed up hair growth and may increase your chance of side effects.

What kind of shampoo should I use with Toppik Men's Hair Regrowth Treatment Extra Strength?

If you wash your scalp before applying Toppik Men's Hair Regrowth Treatment Extra Strength, use a mild shampoo.

Can I use hair sprays, mousses, conditioners, gels, etc.?

Yes. Hair sprays, spritzes, or styling aids may be used on your hair while using Toppik Men's Hair Regrowth Treatment Extra Strength. For best results, Toppik Men's Hair Regrowth Treatment Extra Strength should be allowed to soak into the scalp before using any styling products. Try to develop a good routine of applying Toppik Men's Hair Regrowth Treatment Extra Strength first, and then applying styling products and style as usual. Keep in mind that your best results will be seen with proper application.

Can I have my hair colored or permed or use hair relaxers while using Men's Toppik Men's Hair Regrowth Treatment Extra Strength?

Yes. We have no evidence that coloring or perming your hair or that the use of relaxers change the effect of Toppik Men's Hair Regrowth Treatment Extra Strength. However, because the use of a permanent wave and hair color can cause scalp irritation on certain people, we recommend the following precautions:

1. To avoid possible scalp irritation, you should make sure all of the Toppik Men's Hair Regrowth Treatment Extra Strength has been washed off the hair and scalp before using color or perm chemicals.
2. For best results, do not apply Toppik Men's Hair Regrowth Treatment Extra Strength on the same day that you use a chemical treatment on your hair.
3. Do not use Toppik Men's Hair Regrowth Treatment Extra Strength for 24 hours after using any chemicals to make sure your scalp has not been irritated by the perm or color treatment. If no irritation occurs, continue use of Toppik Men's Hair Regrowth Treatment Extra Strength as usual.

Simply restart your normal Toppik Men's Hair Regrowth Treatment Extra Strength routine. There is no need to use more Toppik Men's Hair Regrowth Treatment Extra Strength to make up for missed applications. Missing 1 day of Toppik Men's Hair Regrowth Treatment Extra Strength will not affect your hair regrowth results.

Can I apply Toppik Men's Hair Regrowth Treatment Extra Strength and wash my hair an hour later?

No. For Toppik Men's Hair Regrowth Treatment Extra Strength to work best, you should allow it to stay on the scalp for about 4 hours before washing.

Using the Sprayer Applicator
Important: When applying Toppik Men's Hair Regrowth Treatment, make sure the medicine comes in direct contact with the scalp. The medicine will not work if it is sprayed only on your hair and does not reach your scalp.
Carefully follow the instructions below to use the child-resistant sprayer pump to apply Toppik Men's Hair Regrowth Treatment Extra Strength

1. Remove the bottle of Toppik Men's Hair Regrowth Treatment Extra Strength from the package.
2. Firmly hold the bottle upright with the turning wheel on the back of the bottle facing you. Push in the small tab located to the bottom right of the turning wheel.
3. While holding the tab in, press down on the top of the sprayer and turn the upper part of the sprayer with the turning wheel to the left until the spray nozzle is centered between the beveled grooves on the front of the bottle.
4. Then prime the sprayer by holding the bottle upright and pumping the sprayer 5 times to ensure delivery of a full spray. Be careful not to inhale the mist.
5. Aim the sprayer at your area of thinning hair or hair loss and pump the sprayer 6 times to apply a 1 mL dose twice a day.
6. After applying Toppik Men's Hair Regrowth Treatment Extra Strength, use the turning wheel to turn the sprayer cap back to the right to release the tab which places the sprayer nozzle behind the sprayer cap wall. Make sure the sprayer cannot be pushed or pumped before putting the bottle away.

If pregnant or breast-feeding, ask a health professional before use. Keep out of reach of children.

If swallowed, get medical help or contact a Poison Control Center right away.

What are the most common side effects with Toppik Men's Hair Regrowth Treatment Extra Strength?

The most common side effects are itching and skin irritation of the treated area of the scalp. If scalp irritation continues, stop use and see a doctor. Toppik Men's Hair Regrowth Treatment Extra Strength contains alcohol, which will cause burning or irritation of the eyes. If Toppik Men's Hair Regrowth Treatment Extra Strength accidentally gets into eyes, rinse with large amounts of cool tap water.

If Side Effects Occur: You may report side effects to FDA at 1-800-FDA-1088 or call us at 1-800-THICKEN (844-2536). You can also contact us via email at support@toppik.com or on our website at TOPPIK.com.

Can Toppik Men's Hair Regrowth Treatment Extra Strength produce unwanted hair growth?

Unwanted hair growth on the face and other parts of the body has been reported in women. But it is rare and reversible. If you develop unwanted hair, stop using Toppik Men's Hair Regrowth Treatment Extra Strength. Over time, the unwanted hair, if caused by Toppik Men's Hair Regrowth Treatment Extra Strength, will go away. You can take the following steps to decrease the chances of unwanted hair growth:

1. Limit the application of Toppik Men's Hair Regrowth Treatment Extra Strength only to the scalp;
2. If you use your hands to apply Toppik Men's Hair Regrowth Treatment Extra Strength, wash your hands well immediately afterwards; and
3. After your nighttime application of Toppik Men's Hair Regrowth Treatment Extra Strength, allow enough drying time before going to bed (usually 2 to 4 hours).

Can I use Men's Toppik Men's Hair Regrowth Treatment Extra Strength for baldness or hair loss in babies or children?

No. Toppik Men's Hair Regrowth Treatment Extra Strength must not be used to treat baldness or hair loss in babies and children.

If you have any other questions, ask your health care professional or call us at 1-800-THICKEN (844-2536). You can also contact us via email at support@toppik.com or on our website at TOPPIK.com.

PRINCIPAL DISPLAY PANEL - 60 mL Bottle Canister Label

NDC# 61355-570-60

MEN'S

Clinically proven to help regrow
hair. Reactivates hair follicles
to stimulate regrowth.

Toppik

Hair Regrowth Treatment
5% MINOXIDIL TOPICAL SOLUTION
EXTRA STRENGTH

Easy-To-Use
Spray
Unscented

Not For Use By Women

TOPPIK INC.

60mL (2 fl oz) Bottle/30-Day Supply